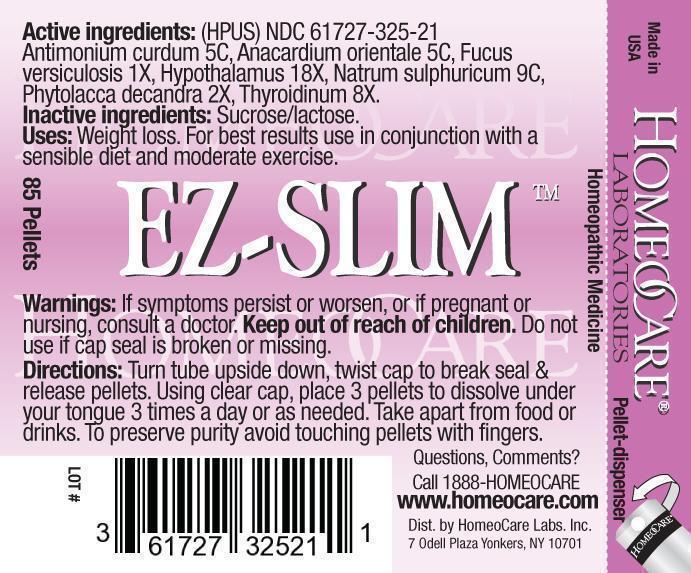 DRUG LABEL: Ez-Slim
NDC: 61727-325 | Form: PELLET
Manufacturer: Homeocare Laboratories
Category: homeopathic | Type: HUMAN OTC DRUG LABEL
Date: 20181231

ACTIVE INGREDIENTS: ANTIMONY TRISULFIDE 5 [hp_C]/4 g; SEMECARPUS ANACARDIUM JUICE 5 [hp_C]/4 g; FUCUS VESICULOSUS 1 [hp_X]/4 g; BOS TAURUS HYPOTHALAMUS 18 [hp_X]/4 g; SODIUM SULFATE 9 [hp_C]/4 g; PHYTOLACCA AMERICANA ROOT 2 [hp_X]/4 g; THYROID, UNSPECIFIED 8 [hp_X]/4 g
INACTIVE INGREDIENTS: SUCROSE; LACTOSE

Ez-Slim

Active Ingredients:

Antimonium curdum 5C, Anacardium orientale 5C, Fucus versiculosis 1X, Hypothalamus 18X, Natrum sulphuricum 9C, Phytolacca decandra 2X, Thyroidinum 8X.

Inactive Ingredients:

Sucrose/lactose.

Purpose:

Weight loss. For best results use in conjunction with a sensible diet and moderate exercise.

Keep out of reach of children.

Indications & Usage:

Turn tube upside down, twist cap to break seal & release pellets. Using clear cap, place 3 pellets to dissolve under your tongue 3 times a day or as needed. Take apart from food or drinks. To preserve purity avoid touching pellets with fingers.

Dosage & Administration:

Turn tube upside down, twist cap to break seal & release pellets. Using clear cap, place 3 pellets to dissolve under your tongue 3 times a day or as needed. Take apart from food or drinks. To preserve purity avoid touching pellets with fingers.

Warnings:

If symptoms persist or worsen, or if pregnant or nursing, consult a doctor. Keep out of reach of children. Do not use if cap seal is broken or missing.

Ez-Slim

Homeopathic Medicine

85 Pellets
hcl_label_EZ-SLIM-2012.jpg